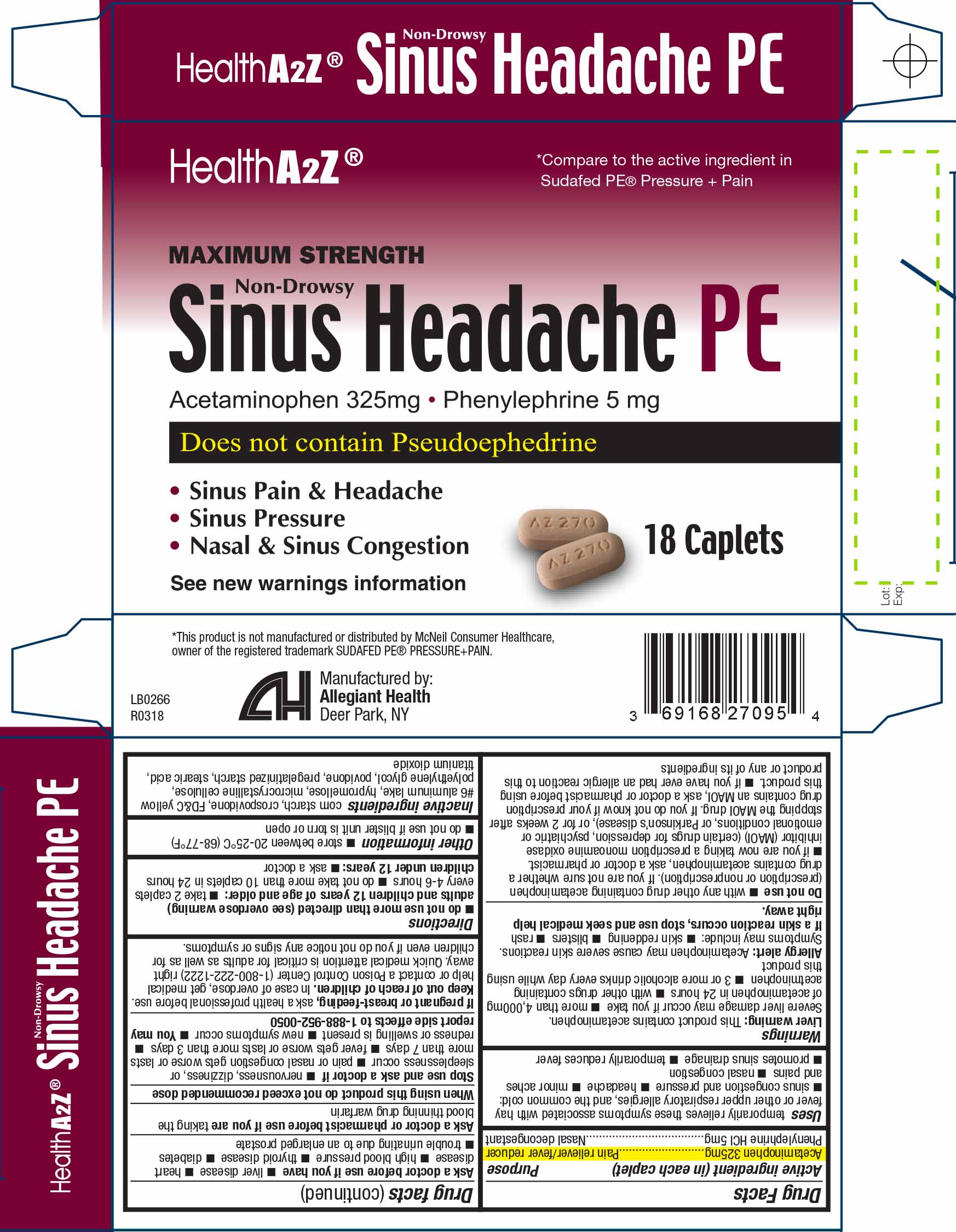 DRUG LABEL: Sinus Headache PEMaximum Strength Non-Drowsy
NDC: 69168-270 | Form: TABLET
Manufacturer: Allegiant Health
Category: otc | Type: HUMAN OTC DRUG LABEL
Date: 20181221

ACTIVE INGREDIENTS: ACETAMINOPHEN 325 mg/1 1; PHENYLEPHRINE HYDROCHLORIDE 5 mg/1 1
INACTIVE INGREDIENTS: STARCH, CORN; FD&C YELLOW NO. 6; HYPROMELLOSES; CELLULOSE, MICROCRYSTALLINE; POLYETHYLENE GLYCOL, UNSPECIFIED; STEARIC ACID; TITANIUM DIOXIDE; CROSPOVIDONE

Drug Facts

Active ingredient (in each caplet)

Acetaminophen 325 mg
Phenylephrine HCl 5 mg

Purpose

Pain reliever/fever reducer
Nasal decongestant

Uses

temporarily relieves these symptoms associated with hay fever or other upper respiratory allergies, and the common cold:

- sinus congestion and pressure
- headache
- minor aches and pains
- nasal congestion
- promotes sinus drainage
- temporarily reduces fever

Warnings

Liver warning/Allergy alert

Liver warning: This product contains acetaminophen.

Severe liver damage may occur if you take

- more than 4,000mg of acetaminophen in 24 hours
- with other drugs containing acetminophen
- 3 or more alcoholic drinks every day while using this product

Allergy alert: Acetaminophen may cause severe skin reactions.

Symptoms may include:

- skin reddening
- blisters
- rash

If a skin reaction occurs, stop use and seek medical help right away.

Do not use

- with any other drug containing acetaminophen (prescription or nonprescription). If you are not sure whether a drug contains acetaminophen, ask a doctor or pharmacist.
- if you are now taking a prescription monoamine oxidase inhibitor (MAOI) (certain drugs for depression, psychiatric or emotional conditions, or Parkinson’s disease), or for 2 weeks after stopping the MAOI drug. If you do not know if your prescription drug contains an MAOI, ask a doctor or pharmacist before using this product.
- if you have ever had an allergic reaction to this product or any of its ingredients

Ask a doctor before use if you have

- liver disease
- heart disease
- high blood pressure
- thyroid disease
- diabetes
- trouble urinating due to an enlarged prostate

Ask a doctor or pharmacist before use if you are

taking the blood thinning drug warfarin

When using this product do not exceed recommended dose

Stop use and ask a doctor if

- nervousness, dizziness, or sleeplessness occur
- pain or nasal congestion gets worse or lasts more than 7 days
- fever gets worse or lasts more than 3 days
- redness or swelling is present
- new symptoms occur
- You may report side effects to 1-888-952-0050

If pregnant or breast-feeding, ask a health professional before use.

Keep out of reach of children. In case of overdose, get medical help or contact a Poison Control Center (1-800-222-1222) right away. Quick medical attention is critical for adults as well as for children even if you do not notice any signs or symptoms.

Directions

do not use more than directed (see overdose warning)

adults and children 12 years of age and older:

- take 2 caplets every 4-6 hours
- do not take more than 10 caplets in 24 hours

children under 12 years:

- ask a doctor

Inactive Ingredients

corn starch, crospovidone, FD&C yellow #6 aluminum lake, hypromellose, microcrystalline cellulose, polyethylene glycol, povidone, pregelatinized starch, stearic acid, titanium dioxide

Package/Label Principal Display Panel

Sinus Headache